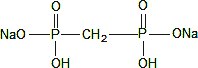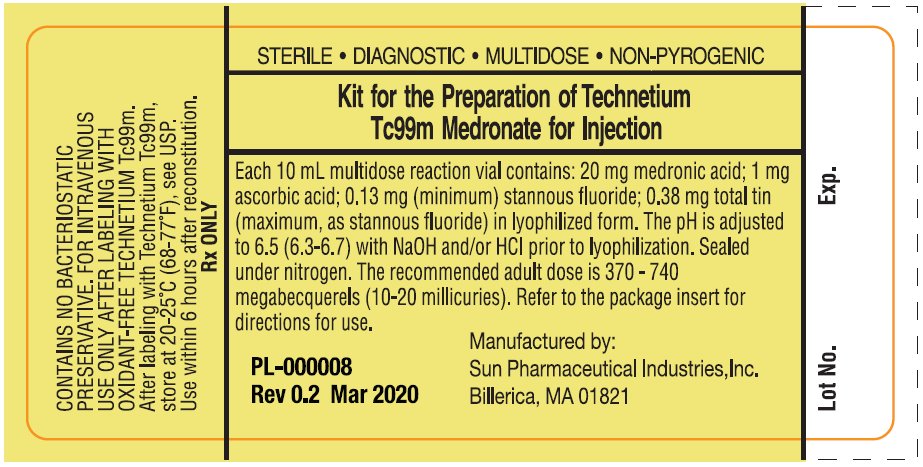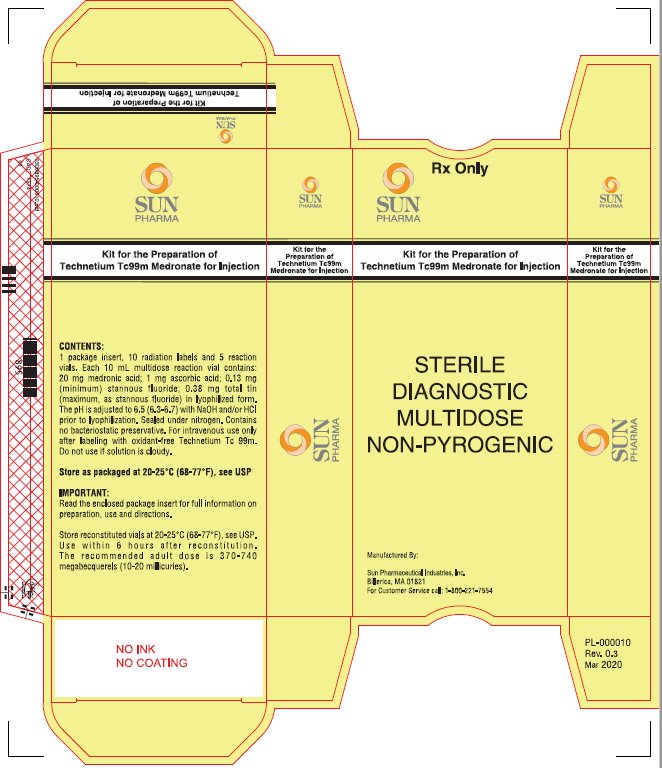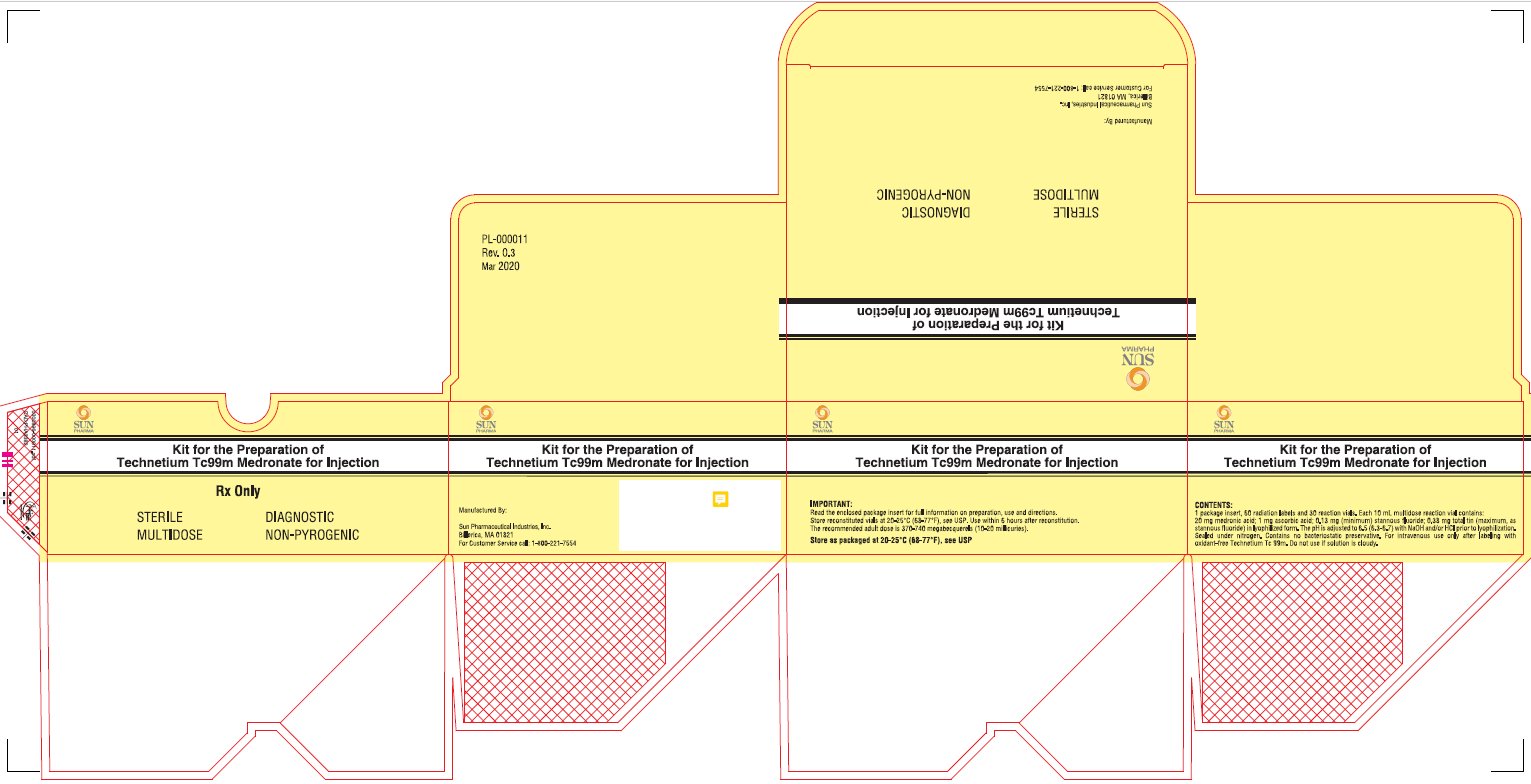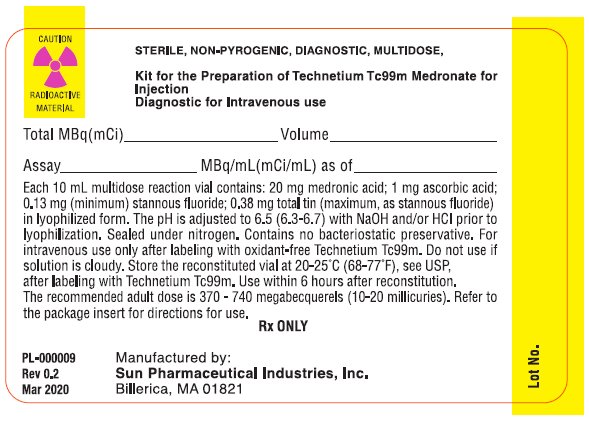 DRUG LABEL: Kit for the Preparation of Technetium Tc 99M Medronate
NDC: 45567-0040 | Form: INJECTION, POWDER, LYOPHILIZED, FOR SOLUTION
Manufacturer: Sun Pharmaceutical Industries, Inc.
Category: prescription | Type: HUMAN PRESCRIPTION DRUG LABEL
Date: 20250311

ACTIVE INGREDIENTS: TECHNETIUM TC-99M MEDRONATE 20 mg/10 mL
INACTIVE INGREDIENTS: ASCORBIC ACID 1 mg/10 mL; STANNOUS FLUORIDE 0.38 mg/10 mL

Kit for the Preparation of
Technetium Tc 99m Medronate for Injection

Description

Kit for the Preparation of Technetium Tc 99m Medronate is a multidose reaction vial which contains the sterile, non-pyrogenic, non-radioactive ingredients necessary to produce Technetium Tc 99m Medronate Injection for diagnostic use by Intravenous injection.

Each 10mL multidose vial contains:

- Medronic acid: 20 mg
- Ascorbic acid: 1 mg
- Stannous fluoride, SnF2: 0.13 mg (minimum)
- Total tin (maximum, as stannous fluoride, SnF2): 0.38 mg

The pH is adjusted to 6.5 (6.3 to 6.7) with sodium hydroxide and/or hydrochloric acid prior to lyophilization. No bacteriostatic preservative is present in the vial. The contents of the vial are lyophilized and sealed under nitrogen at the time of manufacture. The structural formula is:

When a solution of sterile, non-pyrogenic, oxidant-free Sodium Pertechnetate Tc 99m Injection is added to the vial, the diagnostic agent, Technetium Tc 99m Medronate is formed for administration by intravenous injection. The pH of the reconstituted product is 5.4 to 6.8. The precise structure of Technetium Tc 99m Medronate Injection is not known at this time.

PHYSICAL CHARACTERISTICS:

Technetium Tc 99m decays by isomeric transition with a physical half-life of 6.02 hours^1. The principal photon that is useful for detection and imaging studies is listed in Table 1.

TABLE 1 Principal Radiation Emission Data
Radiation | Mean % per Disintegration | Mean Energy (keV)
Gamma-2 | 89.07 | 140.5

^1Kocher, DC: Radioactive Decay Data Tables, DOE/TIC-11026, 108, 1981.

EXTERNAL RADIATION:

The specific gamma ray constant for Tc 99m is 0.78 R/millicurie-hr at 1 cm. The first half-value layer is 0.017 cm of lead (Pb). A range of values for the relative attenuation of the radiation emitted by this radionuclide that results from interposition of the various thicknesses of Pb is shown in Table 2. To facilitate control of the radiation exposure from millicurie amounts of this radionuclide, the use of a 0.25 cm thickness of Pb will attenuate the radiation emitted by a factor of about 1,000.

TABLE 2 Radiation Attenuation by Lead Shielding
Shield Thickness (Pb) cm | Coefficient of Attenuation
0.017 | 0.5
0.08 | 10^-1
0.16 | 10^-2
0.25 | 10^-3
0.33 | 10^-4

To correct for physical decay of this radionuclide, the fractions that remain at selected intervals after the time of calibration are shown in Table 3.

TABLE 3 Physical Decay Chart: Tc 99m, Half-Life 6.02 Hours
Hours | Fraction Remaining | Hours | Fraction Remaining
0* | 1.000 | 7 | 0.447
1 | 0.891 | 8 | 0.398
2 | 0.794 | 9 | 0.355
3 | 0.708 | 10 | 0.316
4 | 0.631 | 11 | 0.282
5 | 0.562 | 12 | 0.251
6 | 0.501

* Calibration Time

CLINICAL PHARMACOLOGY:

During the initial 24 hours following intravenous injection of Technetium Tc 99m Medronate, about 50% of each dose is retained in the skeleton, and about 50% is excreted in the urine. Upon intravenous injection, Technetium Tc 99m Medronate exhibits a specific affinity for areas of altered osteogenesis. In humans, blood levels fall to 4 to 10% of the injected dose by two hours post-injection and to 3 to 5% by three hours.

Uptake of Technetium Tc 99m Medronate Injection in bone appears to be related to osteogenic activity and to skeletal blood perfusion. The deposition in the skeleton is bilaterally symmetrical, with increased accumulation in the axial structure as compared to the appendicular skeleton. There is increased activity in the distal aspect on long bones as compared to the diaphyses.

INDICATIONS AND USAGE:

Technetium Tc 99m Medronate Injection may be used as a bone imaging agent to delineate areas of altered osteogenesis.

CONTRAINDICATIONS:

None known.

WARNINGS:

This class of compounds is known to complex cations such as calcium. Particular caution should be used with patients who have, or may be predisposed to hypocalcemia (i.e., alkalosis).

Preliminary reports indicate impairment of brain scans using Sodium Pertechnetate Tc 99m Injection which have been preceded by a bone scan using an agent containing stannous ions. The impairment may result in false-positive or false-negative brain scans. It is recommended, where feasible, that brain scans precede bone imaging procedures. Alternatively, a brain imaging agent such as Technetium Tc 99m Pentetate Injection may be employed.

The biodistribution of technetium Tc 99m medronate may be altered in the presence of high levels of certain cations (iron, calcium, and aluminum). This may result in reduced uptake of radionuclide in the skeleton and increased extraosseal uptake, which may potentially degrade imaging quality. High levels of these cations may be caused by concomitant medications or medical conditions (e.g., iron overload, hypercalcemia, etc.). Most cases were observed after iron infusion. (See PRECAUTIONS, Drug Interactions.)

PRECAUTIONS:

General

Contents of the vial are intended only for use in the preparation of Technetium Tc 99m Medronate Injection and are NOTto be administered directly to the patient.

Technetium Tc 99m Medronate Injection as well as other radioactive drugs must be handled with care, and appropriate safety measures should be used to minimize radiation exposure to the patient and clinical personnel consistent with proper patient management.

To minimize radiation dose to the bladder, the patients should be encouraged to drink fluids and to void immediately before the examination and as often thereafter as possible for the next 4 to 6 hours.

Technetium Tc 99m Medronate Injection should be formulated within six (6) hours prior to clinical use. Optimal imaging results are obtained 1 to 4 hours after administration.

The finding of an abnormal concentration of radioactivity implies the existence of underlying pathology, but further study is required to distinguish benign from malignant lesions.

The image quality may be adversely affected by obesity, old age, or impaired renal function.

The components of the kit are sterile and non-pyrogenic. It is essential to follow directions carefully and to adhere to strict aseptic procedures during preparation. Technetium Tc 99m labeling reactions involved depend on maintaining the stannous ion in the reduced state. Hence, Sodium Pertechnetate Tc 99m Injection containing oxidants should not be used.

The preparation contains no bacteriostatic preservative. Technetium Tc 99m Medronate Injection should be stored at 20-25ºC (68-77ºF) and discarded 6 hours after reconstitution. The solution should not be used if the contents are cloudy.

Vials are sealed under nitrogen: air or oxygen is harmful to the contents of the vials and the vials should not be vented.

The components of the Kit for the Preparation of Technetium Tc 99m Medronate for Injection are supplied sterile and non-pyrogenic. Aseptic procedures normally employed in making additions and withdrawals for sterile, non-pyrogenic containers should be used during addition of the pertechnetate solution and the withdrawal of doses for patient administration. Shielding should be utilized when preparing Technetium Tc 99m Medronate Injection.

No special handling is required for the non-radioactive drug product.

Radiopharmaceuticals should be used only by physicians who are qualified by training and experience in the safe use and handling of radionuclides, and whose experience and training have been approved by the appropriate government agency authorized to license the use of radionuclides.

Drug Interactions

The biodistribution of technetium Tc 99m medronate may be altered in the presence of high levels of certain cations (iron, calcium, and aluminum). This may result in reduced uptake of radionuclide in the skeleton and increased extraosseal uptake, which may potentially degrade imaging quality. In patients with high levels of these cations caused by concomitant medications, particularly patients receiving iron infusions, consider performing an imaging study with technetium Tc 99m medronate injection once the cation levels have normalized (e.g., after 3 to 5 half-lives of the cation). (See WARNINGS.)

Carcinogenesis, Mutagenesis, Impairment of Fertility

No long-term animal studies have been performed to evaluate carcinogenic potential or whether Technetium Tc 99m Medronate Injection affects fertility in males or females. Mutagenesis studies have not been conducted.

Pregnancy

Animal reproduction and teratogenicity studies have not been conducted on Technetium Tc 99m Medronate Injection. It is also not known whether Technetium Tc 99m Medronate Injection can cause fetal harm when administered to a pregnant woman or can affect reproductive capacity. Technetium Tc 99m Medronate Injection should be given to a pregnant woman only if clearly needed.

Ideally, examinations using radiopharmaceuticals, especially those elective in nature, on a woman of childbearing capability, should be performed during the first few (approximately 10) days following the onset of menses.

Nursing mothers

Technetium Tc 99m Medronate Injection is excreted in human milk during lactation; therefore, formula feeding should be substituted for breast feeding.

Pediatric Use

Safety and effectiveness in pediatric subjects have not been established.

ADVERSE REACTIONS:

Several adverse reactions due to Technetium Tc 99m Medronate Injection have been reported. These were usually hypersensitivity reactions characterized by itching, various skin rashes, hypotension, chills, nausea, and vomiting. There have also been rare cases of dizziness and asthenia associated with the use of Technetium Tc 99m Medronate.

DOSAGES AND ADMINISTRATION:

Shielding should be utilized when preparing Technetium Tc 99m Medronate Injection.

After preparation with oxidant-free Sodium Pertechnetate Tc 99m Injection, the suggested dose range of Technetium Tc 99m Medronate Injection in the average ADULT patient (70 kg.) is:

- 370-740 megabecquerels: (10-20 millicuries) given intravenously.
- Imaging is optimal at 1 to 4 hours post Injection.

Parenteral drug products should be inspected visually for particulate matter and discoloration prior to administration whenever solution and container permit.

The patient dose should be measured by a suitable radioactivity calibration system immediately prior to administration.

Radiation Dosimetry

The effective half-life was assumed to be the physical half-life for all calculated values. The estimated radiation absorbed doses to an average ADULT patient (70 kg) from an intravenous injection of a maximum of 740 megabecquerels (20 millicuries) of Technetium Tc 99m Medronate Injection are shown in Table 4.

TABLE 4 Estimated Absorbed Radiation Dose^2Technetium Tc 99m Medronate
Organ |  | (MGy/740 MBq) | (Rads / 20 mCi)
Total Body |  | 1.3 | 0.13
Bone Total |  | 7.0 | 0.70
Red Marrow |  | 5.6 | 0.56
Kidneys |  | 8.0 | 0.80
Liver |  | 0.6 | 0.06
Bladder Wall | 2 hour void | 26 | 2.60
 | 4.8 hour void | 62 | 6.20
Ovaries | 2 hour void | 2.4 | 0.24
 | 4.8 hour void | 3.4 | 0.34
Testes | 2 hour void | 1.6 | 0.16
 | 4.8 hour void | 2.2 | 0.22

^2Method of calculation: "S" Absorbed Dose Per Unit Cumulated Activity for Selected Radionuclides and Organs, MIRD Pamphlet No 11 (1975)

HOW SUPPLIED:

Kit for the Preparation of Technetium Tc 99m Medronate Injection is supplied in kits of five (5) or thirty (30) sterile, non-pyrogenic vials. Each 10 mL multidose vial contains 20 mg medronic acid, 1 mg ascorbic acid, 0.13 mg minimum stannous fluoride (SnF2) and 0.38 mg maximum total tin, as stannous fluoride, SnF2in lyophilized form. The pH is adjusted with sodium hydroxide and/or hydrochloric acid prior to lyophilization. The vial does not contain a preservative. The contents of the vial are lyophilized and sealed under nitrogen at the time of manufacture. The pH of the reconstituted product is 5.4 to 6.8.

Kit Contents

Included in each five (5) vial kit is one (1) package insert and ten (10) radiation labels. Included in each thirty (30) vial kit is one (1) package insert and sixty (60) radiation labels.

Storage

Store the product as supplied at 20-25°C (68-77°F) [See USP]. After reconstitution store at 20-25°C (68-77°F) [See USP] (see DOSAGE AND ADMINISTRATION).

DIRECTIONS FOR PREPARATION OF TECHNETIUM Tc 99m MEDRONATE INJECTION:

Procedural Precautions

The lyophilized powder in the reaction vial is sterile and non-pyrogenic and does not contain a preservative. Shielded syringes and aseptic procedures normally employed in making additions and withdrawals from sterile, non-pyrogenic containers should be used during addition of pertechnetate solution to the reaction vial and the withdrawal of doses for patient administration.

If sodium pertechnetate Tc 99m must be diluted prior to injection into the reaction vial, only Sodium Chloride Injection USP 0.9% (without preservatives) should be used.

Technetium Tc 99m Medronate Injection is prepared from Kit for the Preparation of Technetium Tc 99m Medronate for Injection by the following aseptic procedure:

1. Waterproof gloves should be worn during the preparation procedure. Remove the plastic disk from the vial and swab the top of the vial closure with alcohol to sanitize the surface.
2. Complete the radiation label and affix to the vial. Place the reaction vial in a suitable radiation shield.
3. With a sterile, shielded syringe aseptically obtain 0.5-5 mL, of a suitable, oxidant-free, sterile, non-pyrogenic Sodium Pertechnetate Tc 99m Injection containing no more than 18.5 gigabecquerels (500 millicuries). Aseptically add the Sodium Pertechnetate Tc 99m Injection to the vial. Be sure to maintain a nitrogen atmosphere in the vial by not introducing air during reconstitution.
4. Swirl the contents of the vial for one minute, and let stand for at least 10 minutes.
5. Record time and date of preparation.
6. The radiochemical purity of the prepared radiopharmaceutical should be checked prior to patient administration.
7. Examine vial contents for particulates and discoloration prior to injection. Do not use if solution is cloudy.
8. Withdrawals for administration must be made aseptically using a sterile shielded syringe and needle. Since the vials contain nitrogen to prevent oxidation of the complex, the vials should not be vented. If repeated withdrawals are made from a vial, the replacement of contents with air should be minimized.
9. Use within six (6) hours of preparation. For optimum results, this time should be minimized. The vial contains no bacteriostatic preservative. After reconstitution store at 20-25°C (68-77°F) [See USP].
10. The patient dose should be measured by a suitable radioactivity calibration system immediately prior to administration.

NDC# 045567-0040-1 (5 vial pack)

NDC# 045567-0040-2 (30 vial pack)

This reagent kit for the preparation of a radiopharmaceutical is approved for use by persons licensed pursuant to Section 120.547, Code of Massachusetts Regulation 105, or under equivalent license of the U.S. Nuclear Regulatory Commission or an Agreement State.

Manufactured By:

Sun Pharmaceutical Industries, Inc.

Billerica, MA 01821

1-800-221-7554

(For International, call 781-275-7120)

PL-000007

Rev 2

Feb 2025

PACKAGE LABEL - PRINCIPAL DISPLAY PANEL - 5 VIAL CONTAINER

NDC045567-0040-1

Sun Pharmaceutical Industries, Inc.

Kit for the Preparation of Technetium Tc99m Medronate for Injection

Rx Only

STERILE

DIAGNOSTIC

MULTIDOSE

NON-PYROGENIC

Each 10mL multidose reaction vial contains: 20 mg medronic acid; 1 mg ascorbic acid; 0.13mg (minimum) stannous fluoride; 0.38 mg total tin (maximum, as stannous fluoride) in lyophilized form. The pH is adjusted to 6.5 (6.3 - 6.7) with NaOH and/or HCI prior to lyophilization. Sealed under nitrogen. The recommended adult dose is 370 - 740 megabecquerels (10-20 millicuries). Refer to the package insert for directions for use.

CONTAINS NO BACTERIOSTATIC PRESERVATIVE. FOR INTRAVENOUS USE ONLY AFTER LABELING WITH OXIDANT-FREE TECHNETIUM Tc99m. After labeling with Technetium Tc99m, store at 20-25°C (68-77°F), see USP. Use within 6 hours after reconstitution.

10 mL

Manufactured By:

Sun Pharmaceutical Industries, Inc.

Billerica, MA 01821

PL-000008

Rev 0.2

Mar 2020

PACKAGE LABEL - PRINCIPAL DISPLAY PANEL - 5 VIAL CARTON

NDC045567-0040-1

Sun Pharmaceutical Industries, Inc.

Kit for the Preparation of Technetium Tc99m Medronate for Injection

Rx Only

STERILE

DIAGNOSTIC

MULTIDOSE

NON-PYROGENIC

CONTENTS:

1 Package insert, 10 radiation labels and 5 reaction vials. Each 10 mL multidose reaction vial contains: 20 mg medronic acid; 1 mg ascorbic acid, 0.13 mg (minimum) stannous fluoride; 0.38 mg total tin (maximum, as stannous fluoride) in lyophilized form. The pH is adjusted to 6.5 (6.3-6.7) with NaOH and/or HCI prior to lyophilization. Sealed under nitrogen. Contains no bacteriostatic preservative. For intravenous use only after labeling with oxidant-free Technetium Tc 99m. Do not use if solution is cloudy.

Store as packaged at 20-25°C (68-77°F), see USP

IMPORTANT:

Read the enclosed package insert for full information on preparation, use and directions.

Store reconstituted vials at 20-25°C (68-77°F), see USP. Use within 6 hours after reconstitution.

The recommended adult dose is 370-740 megabecquerels (10-20 millicuries).

Manufactured By:

Sun Pharmaceutical Industries, Inc.

Billerica, MA 01821

PL-000010

Rev 0.3

Mar 2020

PACKAGE LABEL - PRINCIPAL DISPLAY PANEL - 30 VIAL CONTAINER

NDC045567-0040-2

Sun Pharmaceutical Industries, Inc.

Kit for the Preparation of Technetium Tc99m Medronate for Injection

Rx Only

STERILE

DIAGNOSTIC

MULTIDOSE

NON-PYROGENIC

Each 10mL multidose reaction vial contains: 20 mg medronic acid; 1 mg ascorbic acid; 0.13mg (minimum) stannous fluoride; 0.38 mg total tin (maximum, as stannous fluoride) in lyophilized form. The pH is adjusted to 6.5 (6.3 - 6.7) with NaOH and/or HCI prior to lyophilization. Sealed under nitrogen. The recommended adult dose is 370 - 740 megabecquerels (10-20 millicuries). Refer to the package insert for directions for use.

CONTAINS NO BACTERIOSTATIC PRESERVATIVE. FOR INTRAVENOUS USE ONLY AFTER LABELING WITH OXIDANT-FREE TECHNETIUM Tc99m. After labeling with Technetium Tc99m, store at 20-25°C (68-77°F), see USP. Use within 6 hours after reconstitution.

10 mL

Manufactured By:

Sun Pharmaceutical Industries, Inc.

Billerica, MA 01821

PL-000008

Rev 0.2

Mar 2020

PACKAGE LABEL - PRINCIPAL DISPLAY PANEL - 30 VIAL CARTON

NDC045567-0040-2

Sun Pharmaceutical Industries, Inc.

Kit for the Preparation of Technetium Tc99m Medronate for Injection

Rx Only

STERILE

DIAGNOSTIC

MULTIDOSE

NON-PYROGENIC

CONTENTS:

1 Package insert, 60 radiation labels and 30 reaction vials. Each 10 mL multidose reaction vial contains: 20 mg medronic acid; 1 mg ascorbic acid, 0.13 mg (minimum) stannous fluoride; 0.38 mg total tin (maximum, as stannous fluoride) in lyophilized form. The pH is adjusted to 6.5 (6.3-6.7) with NaOH and/or HCI prior to lyophilization. Sealed under nitrogen. Contains no bacteriostatic preservative. For intravenous use only after labeling with oxidant-free Technetium Tc 99m. Do not use if solution is cloudy.

Store as packaged at 20-25°C (68-77°F), see USP

IMPORTANT:

Read the enclosed package insert for full information on preparation, use and directions.

Store reconstituted vials at 20-25°C (68-77°F), see USP. Use within 6 hours after reconstitution.

The recommended adult dose is 370-740 megabecquerels (10-20 millicuries).

Manufactured By:

Sun Pharmaceutical Industries, Inc.

Billerica, MA 01821

PL-000011

Rev 0.3

Mar 2020

PACKAGE LABEL – PRINCIPAL DISPLAY PANEL – RADIATION SHIELD

CAUTION RADIOACTIVE MATERIAL

STERILE, NON-PYROGENIC, DIAGNOSTIC, KIT FOR THE PREPARATION OF TECHNETIUM Tc 99m MEDRONATE INJECTION DIAGNOSTIC FOR INTRAVENOUS USE

Total MBq (mCi)____Volume_____

Assay_____MBq/mL(mCi/mL) as of_____

Each 10 mL multidose reaction vial contains: 20 mg medronic acid; 1 mg ascorbic acid; 0.13 mg (minimum) stannous fluoride; 0.38 mg total tin (maximum, as stannous fluoride) in lyophilized form. The pH is adjusted to 6.5 (6.3 – 6.7) with NaOH and/or HCl prior to lyophilization. Sealed under nitrogen. Contains no bacteriostatic preservative. For intravenous use only after labeling with oxidant-free Technetium Tc99m. Do not use if solution is cloudy. Store the reconstituted vial at 20-25°C (68-77°F), see USP, after labeling with Techneitum Tc99m. Use within 6 hours after reconstitution. The recommended adult dose is 370 – 740 megabecquerels (10-20 millicuries). Refer to the package insert for directions for use.

(SEE ENCLSOED PACKAGE INSERT)

Rx ONLY

Manufactured by:

Sun Pharmaceutical Industries, Inc.

Billerica, MA 01821

PL-000009

Rev 0.2

Mar 2020